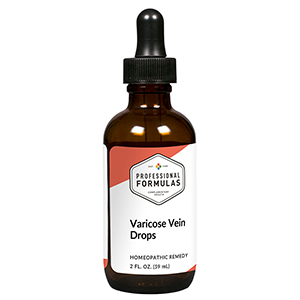 DRUG LABEL: Varicose Vein Drops
NDC: 63083-2151 | Form: LIQUID
Manufacturer: Professional Complementary Health Formulas
Category: homeopathic | Type: HUMAN OTC DRUG LABEL
Date: 20190815

ACTIVE INGREDIENTS: HAMAMELIS VIRGINIANA ROOT BARK/STEM BARK 1 [hp_X]/59 mL; MANGIFERA INDICA BARK 1 [hp_X]/59 mL; LYCOPERDON UTRIFORME FRUITING BODY 3 [hp_X]/59 mL; CALCIUM IODIDE 3 [hp_X]/59 mL; MILK THISTLE 3 [hp_X]/59 mL; ACHILLEA MILLEFOLIUM WHOLE 3 [hp_X]/59 mL; CALCIUM FLUORIDE 6 [hp_X]/59 mL; ACTIVATED CHARCOAL 12 [hp_X]/59 mL; CAULOPHYLLUM THALICTROIDES ROOT 12 [hp_X]/59 mL; CLEMATIS RECTA FLOWERING TOP 12 [hp_X]/59 mL; VIPERA BERUS VENOM 15 [hp_X]/59 mL
INACTIVE INGREDIENTS: ALCOHOL; WATER

C151

ACTIVE INGREDIENTS

Hamamelis virginiana 1X
Mangifera indica 1X
Bovista 3X
Calcarea iodata 3X
Carduus marianus 3X
Millefolium 3X
Calcarea fluorica 6X
Carbo vegetabilis 12X
Caulophyllum thalictroides 12X
Clematis erecta 12X
Hydrofluoricum acidum 12X
Vipera torva 15X

QUESTIONS

Professional Formulas

PO Box 2034 Lake Oswego, OR 97035

INDICATIONS

For the temporary relief of aches, pains, swelling, itchiness, or bruising associated with varicose veins.*

PURPOSE

*Claims based on traditional homeopathic practice, not accepted medical evidence. Not FDA evaluated.

WARNINGS

In case of overdose, get medical help or contact a poison control center right away.

Keep out of the reach of children.

PREGNANCY OR BREAST FEEDING

If pregnant or breastfeeding, ask a healthcare professional before use.

DIRECTIONS

Place drops under tongue 30 minutes before/after meals. Adults and children 12 years and over: Take 10 drops up to 3 times per day. Consult a physician for use in children under 12 years of age.

OTHER INFORMATION

Tamper resistant. If seal is broken, do not use. After opening, close container tightly and store at room temperature away from heat.

INACTIVE INGREDIENTS

20% ethanol, purified water.

LABEL

Est 1985

Professional Formulas

Complementary Health

Varicose Vein Drops

Homeopathic Remedy

2 FL. OZ. (59 mL)